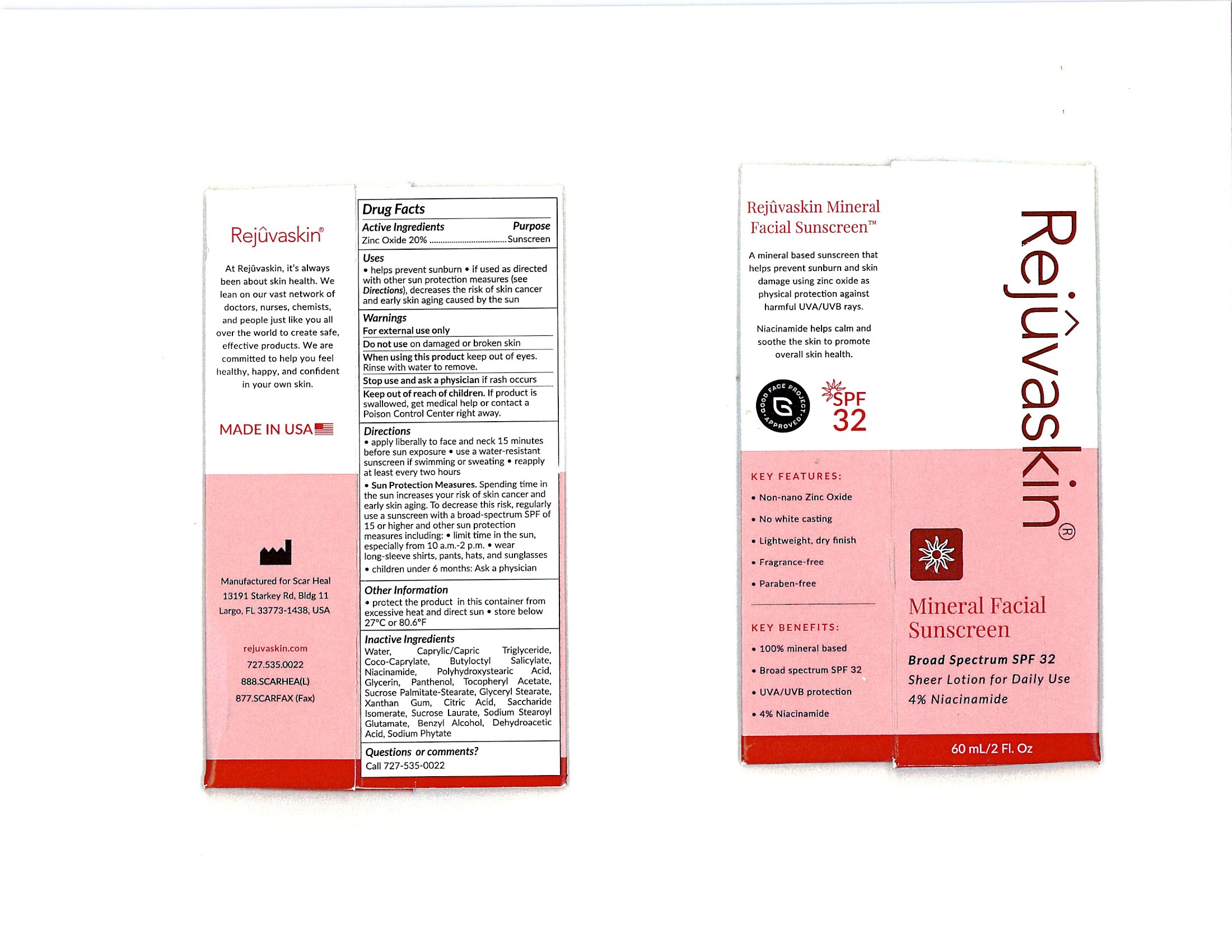 DRUG LABEL: Rejuvaskin Mineral Facial Sunscreen SPF 32 Sheer
NDC: 84375-101 | Form: LOTION
Manufacturer: Atlantic Medical Products , LLC
Category: otc | Type: HUMAN OTC DRUG LABEL
Date: 20240605

ACTIVE INGREDIENTS: ZINC OXIDE 20 g/100 g
INACTIVE INGREDIENTS: DEHYDROACETIC ACID; NIACINAMIDE; GLYCERYL MONOSTEARATE; COCO-CAPRYLATE; SUCROSE STEARATE; XANTHAN GUM; WATER; MEDIUM-CHAIN TRIGLYCERIDES; CITRIC ACID MONOHYDRATE; PANTHENOL; POLYHYDROXYSTEARIC ACID (2300 MW); PHYTATE SODIUM; SACCHARIDE ISOMERATE; GLYCERIN; SODIUM STEAROYL GLUTAMATE; SUCROSE STEARATE/PALMITATE ESTER (75% MONO ESTER); .ALPHA.-TOCOPHEROL ACETATE; SUCROSE LAURATE

Rejuvaskin Mineral Facial Sunscreen Broad Spectrum SPF32 Sheer lotion for daily use 4% Niacinamide (IS0122-7)

Active ingredients

Zinc Oxide 20%.......................................Sunscreen

When using this Product keep out of eyes. Rise with water to remove.

WARNINGS

For external use only.

Stop use and ask a physician if rash occurs.

Keep out of reach of children. If product is swallowed, get medical help or contact a Poison Control Center right away.

Do not use section on damaged or broken skin

Inactive Ingredients

Benzyl Alcohol

Butyloctyl Salicylate

Caprylic/Capric Triglyceride

Citric Acid

Coco-Caprylate

Dehydroacetic Acid

Glycerin

Glyceryl Stearate

Niacinamide

Panthenol

Polyhydroxystearic Acid

Sodium Phytate

Saccharide Isomerate

Sodium Stearoyl Glutamate

Sucrose palmitate-stearate

Sucrose Laurate

Tocopheryl Acetate

Water

Xanthan Gum

PURPOSE

Acrive Ingredients

Zinc Oxide 20%.......................................Sunscreen

INDICATIONS AND USAGE

Uses helps prevent sunburn

if used directed with other sun protection measures(see Directions),decreases the risk of skin cancer and early agung caused by the sun.

Directions

- Apply liberally to face and neck 15 minutes before sun exposure
- use a water-resistant sunscreen if swimming or sweating
- reapply at leat every two hours
- Sun Protection measures Spending time in the sun increase your risk of skin cancer and early skin aging. To decrease this risk, regularly use a sunscreen with a broad-spectrum SPF of 15 or higher and other sun protection measures including
- limit time in the sun, especially from 10 am- 2 pm
- wear long-sleeve shirts, pants, hats, and sunglasses
- children under 6 months: Ask a physician